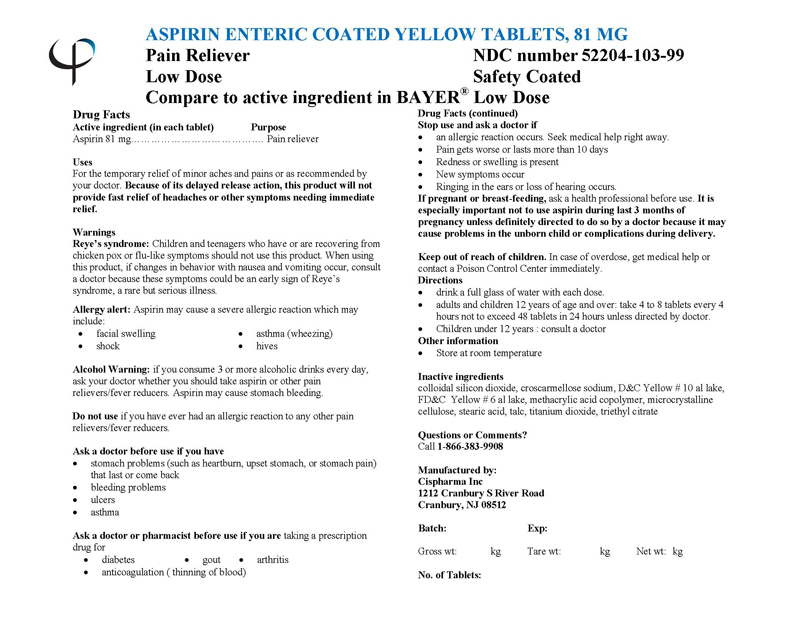 DRUG LABEL: ASPIRIN
NDC: 52204-103 | Form: TABLET, COATED
Manufacturer: Cispharma, Inc
Category: otc | Type: HUMAN OTC DRUG LABEL
Date: 20110417

ACTIVE INGREDIENTS: ASPIRIN 81 mg/1 1
INACTIVE INGREDIENTS: SILICON DIOXIDE; CROSCARMELLOSE SODIUM; D&C YELLOW NO. 10; FD&C YELLOW NO. 6; METHACRYLIC ACID - ETHYL ACRYLATE COPOLYMER (1:1) TYPE A; MICROCRYSTALLINE WAX; STEARIC ACID; TALC; TITANIUM DIOXIDE; TRIETHYL CITRATE

ASPIRIN ENTERIC COATED YELLOW TABLETS, 81 mg

Drug Facts

Active ingredient (in each tablet)

Aspirin (NSAID*) .............................. 81 mg

*Nonsteroidal anti-inflammatory drug

PURPOSE

Pain Reliever

Uses

For the temporary relief of minor aches and pains or as recommended by your doctor. Because of its delayed release action, this product will not provide fast relief of headaches or other symptoms needing immediate relief.

Warnings

Reye's syndrome: Children and teenagers who have or are recovering from chicken pox or flu-like symptoms should not use this product. When using this product, if changes in behavior with nausea and vomiting occur, consult a doctor because these symptoms could be an early sign of Reye's syndrome, a rare but serious illness.

Allergy alert: Aspirin may cause a severe allergic reaction which may include:

- facial swelling
- asthma (wheezing)
- shock
- hives

Alcohol Warning: if you consume 3 or more alcoholic drinks every day, ask your doctor whether you should take aspirin or other pain relievers/fever reducers. Aspirin may cause stomach bleeding.

Do not use if you have ever had an allergic reaction to any other pain relievers/fever reducers.

Ask a doctor before use if you have

- stomach problems (such as heartburn, upset stomach, or stomach pain) that last or come back
- bleeding problems
- ulcers
- asthma

Ask a doctor or pharmacist before use if you are taking a prescription drug for

- diabetes
- gout
- arthritis
- anticoagulation (thinning of blood)

INDICATIONS AND USAGE

Indicated for pain relief.

Stop use and ask a doctor if

- An allergic reaction occurs. Seek medical help right away
- Pain gets worse or lasts more than 10 days
- Redness or swelling is present
- New symptoms occur
- Ringing in the ears or loss of hearing occurs.

PREGNANCY OR BREAST FEEDING

If pregnant or breast-feeding, ask a health professional before use. It is especially important not to use aspirin during last 3 months of pregnancy unless definitely directed to do so by a doctor because it may cause problems in the unborn child or complications during delivery.

Keep out of reach of children.

OVERDOSAGE

In case of overdose, get medical help or contact a Poison Control Center immediately.

Directions:

- drink a full glass of water with each dose.
- adults and children 12 years of age and over: take 4 to 8 tablets every 4 hours not to exceed 48 tablets in 24 hours unless directed by doctor.
- Children under 12 years: consult a doctor

Other Information

- Store at room temperature

Inactive Ingredients

colloidal silicon dioxide, croscarmellose sodium, D&C Yellow # 10 al lake, FD&C Yellow # 6 al lake, methacrylic acid copolymer, microcrystalline cellulose, stearic acid, talc, titanium dioxide, triethyl citrate

Questions or Comments?
Call 1-866-383-9908

Manufactured by:

Cispharma Inc
1212 Cranbury S River Road
Cranbury, NJ 08512